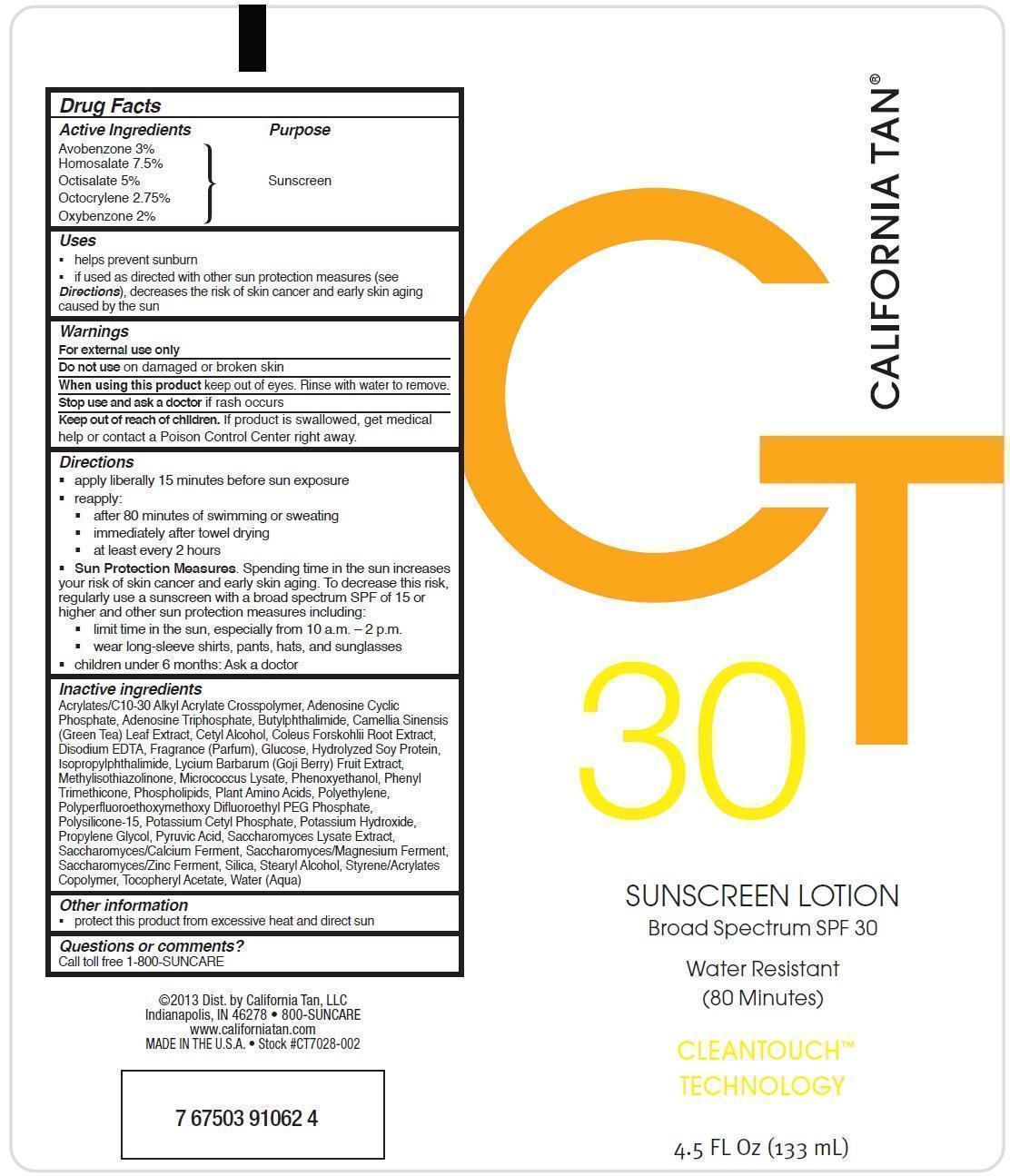 DRUG LABEL: California Tan
NDC: 58443-0096 | Form: LOTION
Manufacturer: Prime Enterprises, Inc.
Category: otc | Type: HUMAN OTC DRUG LABEL
Date: 20200117

ACTIVE INGREDIENTS: AVOBENZONE 29.6 mg/1 mL; HOMOSALATE 73.9 mg/1 mL; OCTISALATE 49.3 mg/1 mL; OCTOCRYLENE 27.1 mg/1 mL; OXYBENZONE 19.7 mg/1 mL
INACTIVE INGREDIENTS: CARBOMER COPOLYMER TYPE A (ALLYL PENTAERYTHRITOL CROSSLINKED); ADENOSINE CYCLIC PHOSPHATE; ADENOSINE TRIPHOSPHATE; BUTYLATED HYDROXYTOLUENE; N-BUTYLPHTHALIMIDE; GREEN TEA LEAF; CETYL ALCOHOL; COLEUS FORSKOHLII ROOT OIL; EDETATE DISODIUM; GLUCOSE OXIDASE; METHYLPARABEN; PHENYL TRIMETHICONE; METHYLISOTHIAZOLINONE; SOY PROTEIN; ISOPROPYLPHTHALIMIDE; N,N-DIMETHYL-2-OCTADECANAMINE; LYCIUM BARBARUM FRUIT; CATALASE (MICROCOCCUS LUTEUS); EGG PHOSPHOLIPIDS; HIGH DENSITY POLYETHYLENE; AMINO ACIDS; POLYSILICONE-15; POTASSIUM CETYL PHOSPHATE; POTASSIUM HYDROXIDE; PROPYLENE GLYCOL; PROPYLPARABEN; PYRUVIC ACID; SACCHAROMYCES LYSATE; CALCIUM; MAGNESIUM; ZINC; SILICON DIOXIDE; STEARYL ALCOHOL; STYRENE

Active ingredients

Avobenzone 3 %. Homosalate 7.5 %, Octisalate 5 %, Octocrylene 2.75 %, and Oxybenzone 2 %

Purpose

Sunscreen

Uses

- helps prevent sunburn
- if used as directed with other sun protection measures (see Directions), decreases the risk of skin cancer and early skin aging caused by the sun

Warnings

OTHER SAFETY INFORMATION

For external use only

Do not use on damaged or broken skin.

When using this product keep out of eyes. Rinse with water to remove.

Stop use and ask a doctor if rash occurs.

Keep out of reach of children. If product is swallowed, get medical help or contact a Poison Control Center right away.

Directions

- apply liberally 15 minutes before sun exposure
- reapply:
  - after 80 minutes of swimming or sweating
  - immediately after towel drying
  - at least every 2 hours
- Sun Protection Measures. Spending time in the sun increases your risk of skin cancer and early skin aging. To decrease this risk, regularly use a sunscreen with a broad spectrum SPF of 15 or higher and other sun protection measures including:
  - limit time in the sun especially from 10 a.m. – 2 p.m.
  - wear long-sleeve shirts, pants, hats, and sunglasses
- children under 6 months: Ask a doctor

Inactive Ingredients

Acrylates/C10-30 Alkyl Acrylate Crosspolymer, Adenosine Cyclic Phosphate, Adenosine Triphosphate, Butylphthalimide, Camellia Sinensis (Green Tea) Leaf Extract, Cetyl Alcohol, Coelus Forskohlii Root Extract, Disodium EDTA, Fragrance (Parfum), Glucose, Hydrolyzed Soy Protein, Isopropylphthalimide, Lycium Barbarum (Goji Berry) Fruit Extract, Methylisothiazolinone, Micrococcus Lysate, Phenoxyethanol, Phenyl Trimethicone, Phospholipids, Plant Amino Acids, Polyethylene, Polyperfluoroethoxymethoxy Difluorohydroxyethyl PEG Phosphate, Polysilicone-15, Potassium Cetyl Phosphate, Potassium Hydroxide, Propylene Glycol, Propylparaben, Saccharomyces Lysate Extract, Saccharomyces/Calcium Ferment, Saccharomyces Magnesium Ferment, Saccharomyces Zinc Ferment, Silica, Stearyl Alcohol, Styrene/Acrylates Copolymer, Tocopheryl Acetate, Water (Aqua)

Other information

- protect this product from excesive heat and direct sun

Questions or Comments?

Call toll free 1-800-SUNCARE

PRINCIPAL DISPLAY PANEL - 133 mL Tube Label

CALIFORNIA TAN

CT

30

SUNSCREEN LOTION

Broad Spectrum SPF 30

Water Resistant

(80 Minutes)

CLEANTOUCH™

TECHNOLOGY

4.5 FL Oz (133 mL)